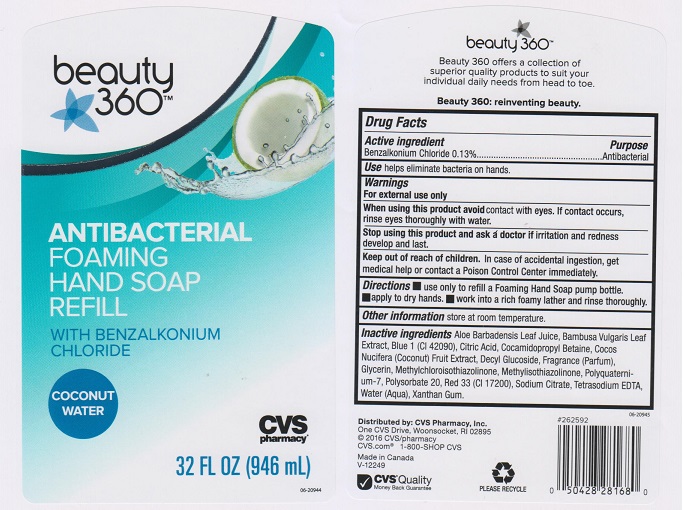 DRUG LABEL: CVS PHARMACY
NDC: 59779-842 | Form: LIQUID
Manufacturer: CVS PHARMACY
Category: otc | Type: HUMAN OTC DRUG LABEL
Date: 20160210

ACTIVE INGREDIENTS: BENZALKONIUM CHLORIDE 1.3 mg/1 mL
INACTIVE INGREDIENTS: ALOE VERA LEAF; BAMBUSA VULGARIS LEAF; FD&C BLUE NO. 1; CITRIC ACID MONOHYDRATE; COCAMIDOPROPYL BETAINE; DECYL GLUCOSIDE; GLYCERIN; METHYLCHLOROISOTHIAZOLINONE; METHYLISOTHIAZOLINONE; POLYQUATERNIUM-7 (70/30 ACRYLAMIDE/DADMAC; 1600000 MW); POLYSORBATE 20; D&C RED NO. 33; SODIUM CITRATE; EDETATE SODIUM; WATER; XANTHAN GUM

DRUG FACTS

Active ingredient

Benzalkonium Chloride 0.13%

Purpose

Antibacterial

Use

- Helps eliminate bacteria on the skin.

Warnings

For external use only.

When using this product

- Avoid contact with eyes. If contact occurs, rinse eyes thoroughly with water.

Stop using this product and ask doctor if

- irritation and redness develop and last.

Keep out of reach of children

- In case of accidental ingestion, get medical help or contact a Poison Control Center immediately.

Directions

- Apply onto dry hands. Work into a lather, rinse and dry thoroughly.

Other information

- Store at room temperature.

Inactive ingredients

Aloe Barbadensis Leaf Juice, Blue 1 (CI 42090), Camellia Sinensis Leaf Extract, Citric Acid, Cocamidopropyl Betaine, Decyl Glucoside, Fragrance (Parfum), Glycerin, Methylchloroisothiazolinone, Methylisothiazolinone, Polyquaternium-7, Polysorbate 20, Red 33 (CI 17200), Sodium Citrate, Tetrasodium EDTA, Water (Aqua), Xanthan Gum